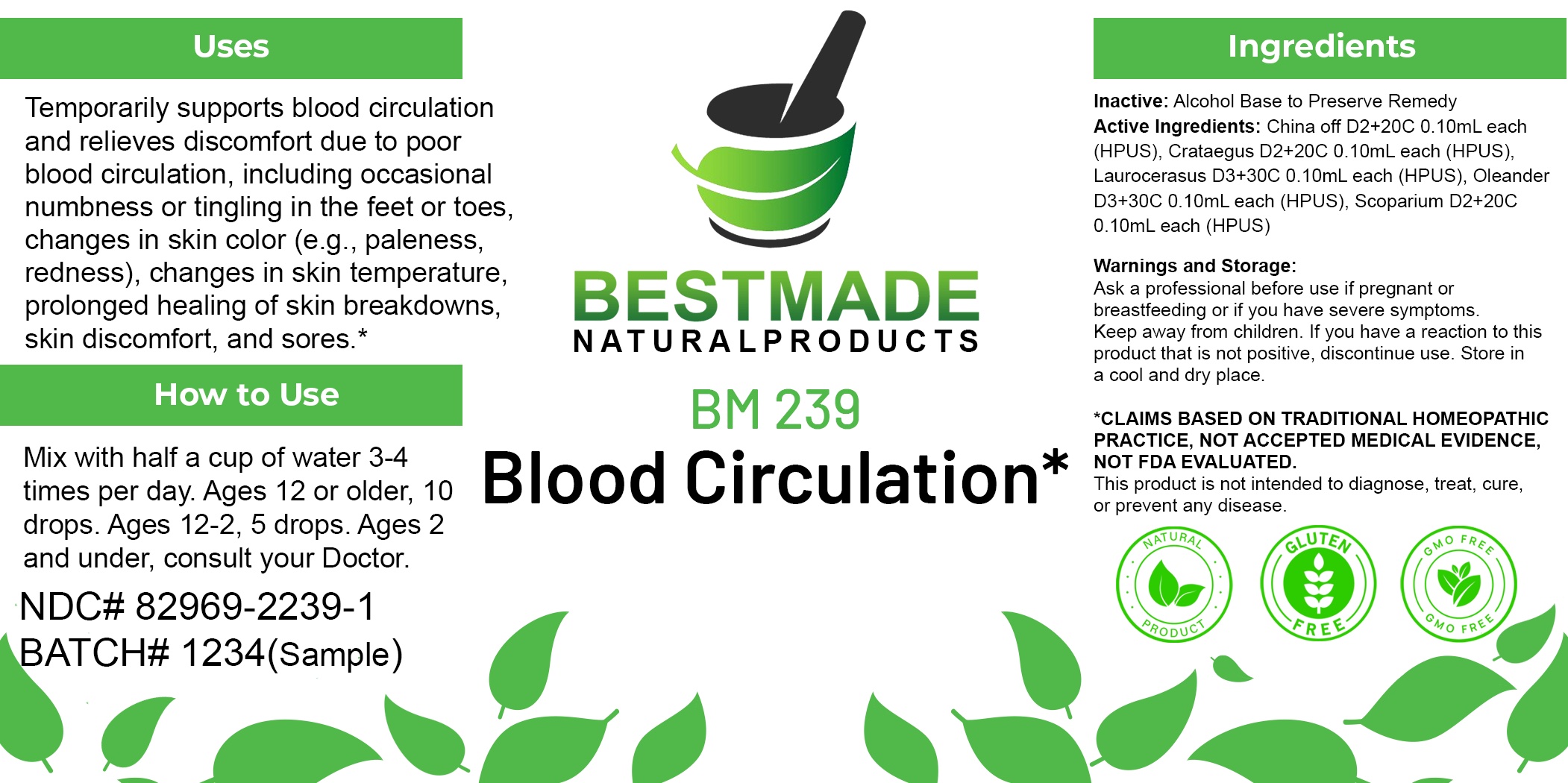 DRUG LABEL: Bestmade Natural Products BM239
NDC: 82969-2239 | Form: LIQUID
Manufacturer: Bestmade Natural Products
Category: homeopathic | Type: HUMAN OTC DRUG LABEL
Date: 20250304

ACTIVE INGREDIENTS: NERIUM OLEANDER LEAF 30 [hp_C]/30 [hp_C]; CYTISUS SCOPARIUS FLOWERING TOP 30 [hp_C]/30 [hp_C]; PRUNUS LAUROCERASUS LEAF 30 [hp_C]/30 [hp_C]; CINCHONA OFFICINALIS BARK 30 [hp_C]/30 [hp_C]; HAWTHORN LEAF WITH FLOWER 30 [hp_C]/30 [hp_C]
INACTIVE INGREDIENTS: ALCOHOL 30 [hp_C]/30 [hp_C]

BM239

DOSAGE AND ADMINISTRATION

How to Use

Mix with half a cup of water 3-4 times per day. Ages 12 or older, 10 drops. Ages 12-2, 5 drops. Ages 2 and under, consult your Doctor.

Inactive:

Alcohol Base to Preserve Product

ACTIVE INGREDIENT

Active Ingredients: China off D2+20C 0.10mL each (HPUS), Crataegus D2+20C 0.10mL each (HPUS), Laurocerasus D3+30C 0.10mL each (HPUS), Oleander D3+30C 0.10mL each (HPUS), Scoparium D2+20C 0.10mL each (HPUS)

KEEP OUT OF REACH OF CHILDREN

Warnings and Storage:

Ask a professional before use if pregnant or breastfeeding or if you have severe symptoms.

Keep away from children. If you have a reaction to this product that is not positive, discontinue use. Store in a cool and dry place

*CLAIMS BASED ON TRADITIONAL HOMEOPATHIC PRACTICE, NOT ACCEPTED MEDICAL EVIDENCE NOT FDA EVALUATED.
This product is not intended to diagnose, treat, cure, or prevent any disease.

Warnings and Storage:

Ask a professional before use if pregnant or breastfeeding or if you have severe symptoms.

Keep away from children. If you have a reaction to this product that is not positive, discontinue use. Store in a cool and dry place

*CLAIMS BASED ON TRADITIONAL HOMEOPATHIC PRACTICE, NOT ACCEPTED MEDICAL EVIDENCE NOT FDA EVALUATED.
This product is not intended to diagnose, treat, cure, or prevent any disease.

Uses
Temporarily supports blood circulation and relieves discomfort due to poor blood circulation, including occasional numbness or tingling in the feet or toes, changes in skin color (e.g., paleness, redness), changes in skin temperature, prolonged healing of skin breakdowns,
skin discomfort, and sores.*

Uses
Temporarily supports blood circulation and relieves discomfort due to poor blood circulation, including occasional numbness or tingling in the feet or toes, changes in skin color (e.g., paleness, redness), changes in skin temperature, prolonged healing of skin breakdowns,
skin discomfort, and sores.*

Entire package label